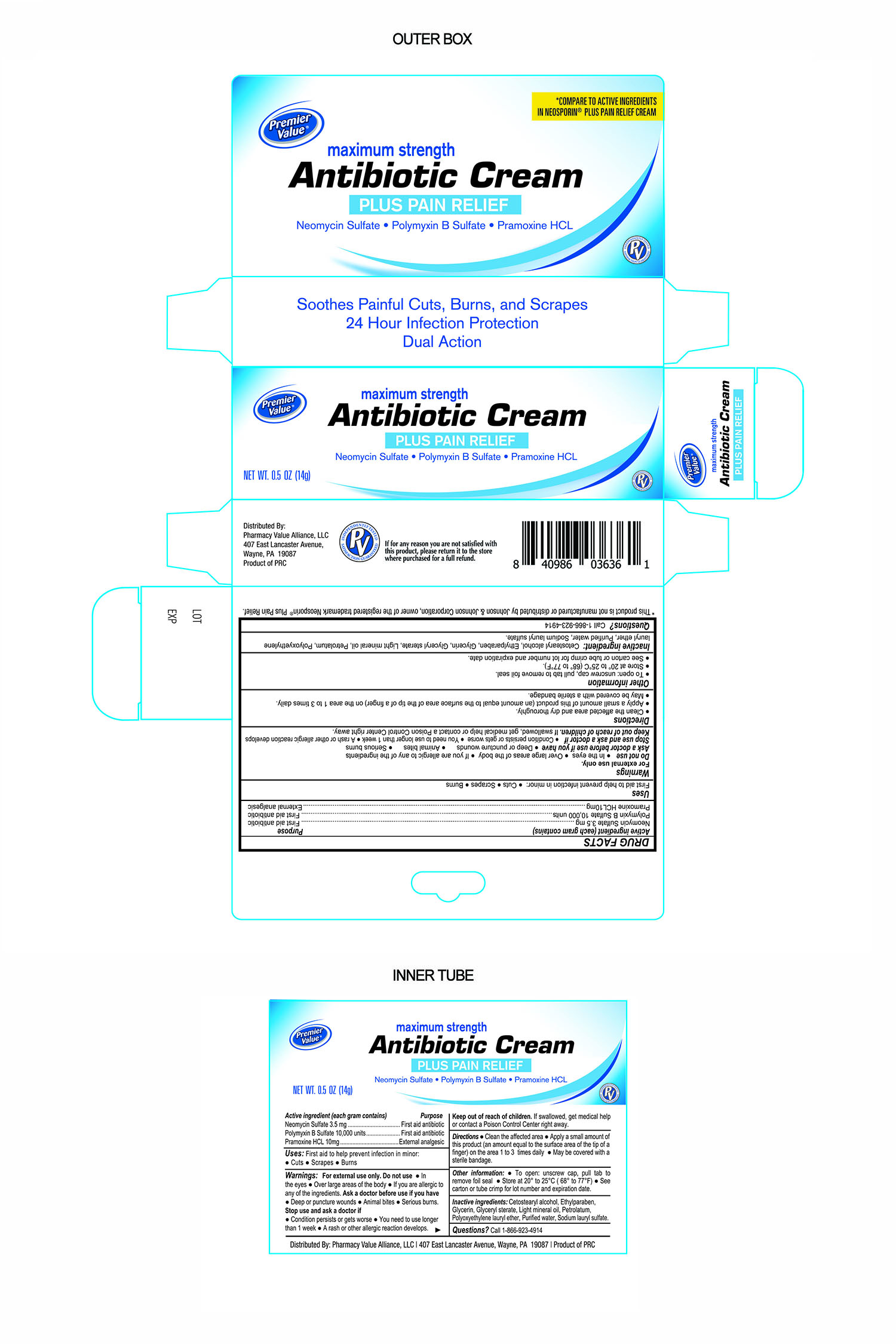 DRUG LABEL: Premier Value Max Strength Antibiotic plus pain relief
NDC: 68016-296 | Form: CREAM
Manufacturer: Pharmacy Value Alliance LLC
Category: otc | Type: HUMAN OTC DRUG LABEL
Date: 20241220

ACTIVE INGREDIENTS: NEOMYCIN SULFATE 3.5 mg/1 g; PRAMOXINE HYDROCHLORIDE 10 mg/1 g; POLYMYXIN B SULFATE 10000 [USP'U]/1 g
INACTIVE INGREDIENTS: SODIUM LAURYL SULFATE; LIGHT MINERAL OIL; SODIUM DODECYLBENZENESULFONATE; PETROLATUM; CETOSTEARYL ALCOHOL; GLYCERIN; GLYCERYL STEARATE SE; WATER; ETHYLPARABEN

Maximum Strength Antibiotic Cream plus Pain Relief

Active Ingredient

Neomycin Sulfate 3.5mg

Purpose

First Aid Antibiotic

Active Ingredient

Polymyxin B Sulfate 10,000 Units

Purpose

First Aid Antibiotic

Active Ingredient

Pramoxine HCL 10mg

Purpose

External Analgesic

Uses

First Aid to help prevent infection in minor:

- Cuts
- Scrapes
- Burns

Warnings

For external use only. Do not use:

- In eyes
- Over large areas of the body
- If you are allergic to any of the ingredients

Ask a Doctor before Use

Ask Doctor before use if you have:

- Deep or puncture wounds
- Animal bites
- Serious burns

Stop Use and ask a Doctor if:

- Condition persists or gets worse
- You need to use longer than 1 week
- A rash or other allergic reaction develops

Keep out of Reach of Children

If Swallowed, get medical help or contact a Poison Control Center right away

Directions

- Clean the affected area and dry thoroughly
- Apply a small amount of this product (an amount equal to the surface area of the tip of a finger) on the area 1 to 3 times daily
- May be covered with a sterile bandage

Other Information

- To Open: Unscrew cap, pull tab to remove foil seal
- Store at 20° to 25°C (68° to 77°F)
- See carton or tube crimp for lot number and expiration date

Inactive Ingredient:

Cetostearyl alcohol, Ethylparaben, Glycerin, Glyceryl Sterate, Light Mineral Oil, Petrolatum, Polyoxyethylene lauryl ether, Purified Water, Sodium Lauryl Sulfate.

Questions or Comments

Call 1-866-923-4914

This product is not manufactured or distributed by Johnson & Johnson Corporation, owner of the regisgtered trademark Neosporin® Plus Pain Relief.

Distributed By:

Pharmacy Value Alliance, LLC.

407 East Lancaster Avenue

Wayne, PA. 19087

Product of PRC